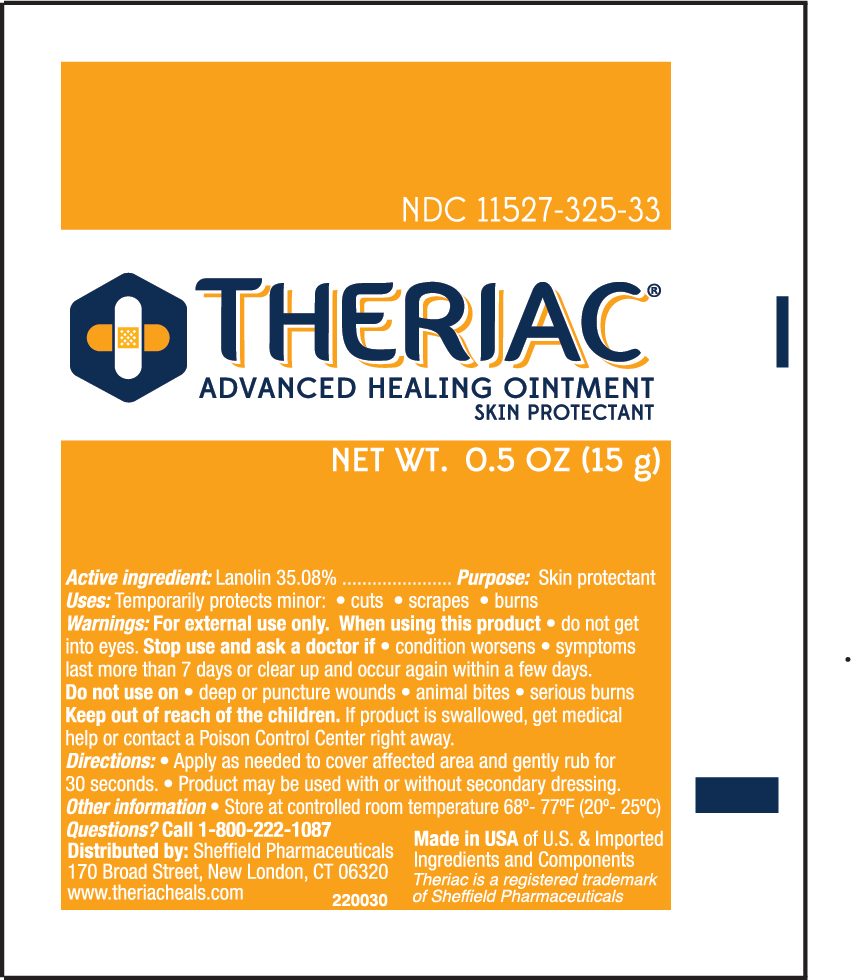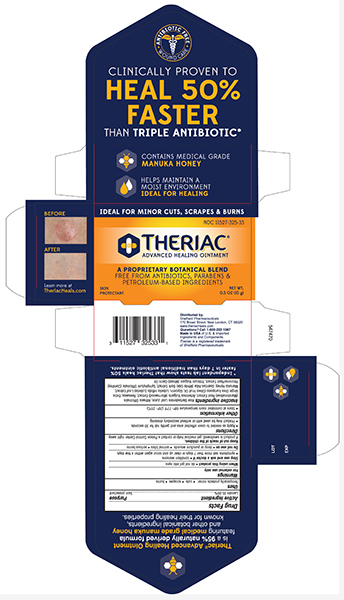 DRUG LABEL: Theriac Advanced Healing
NDC: 11527-325 | Form: OINTMENT
Manufacturer: Sheffield Pharmaceuticals LLC
Category: otc | Type: HUMAN OTC DRUG LABEL
Date: 20231024

ACTIVE INGREDIENTS: LANOLIN 350.8 mg/1 g
INACTIVE INGREDIENTS: ALOE VERA LEAF; ALTHAEA OFFICINALIS ROOT; ARTEMISIA VULGARIS WHOLE; YELLOW WAX; OLIVE OIL; GLYCERIN; LOBELIA INFLATA WHOLE; HONEY; QUERCUS ALBA BARK; SYMPHYTUM OFFICINALE WHOLE; WHEAT GERM OIL

Theriac Advanced Healing Ointment

Drug Facts

Active ingredient

Lanolin 35.08%

Purpose

Skin Protectant

Uses

Temporarily Protects Minor:

- cuts
- scrapes
- burns

Warnings

For external use only

When using this product, do not get into eyes

Stop use and ask a doctor if

- condition worsens
- symptoms last for more thna 7 days or clear up and occur again within a few days.

Do not use on

- deep or puncture wounds
- animal bites
- serious burns

Keep out of reach of children. If product is swallowed, get medical help or contact a Poison Control Center right away.

Directions

- Apply as needed ot the affacted area and gently rub for 30 seconds
- Product may be used with or without secondary dressing.

Inactive ingredients

Aloe Barbadensis Leaf Juice, Althaea Officinalis Root Extract, Artemisia Vulgaris Extract, Beeswax, Extra Virgin Olea Europaea (Olive) Fruit Oil, Glycerin, Lobelia Inflata, Manuka Honey, Quercus Alba Bark Extract, Symphytum Officinale Rhizome/Root Extract , Triticum Vulgare (Wheat) Germ Oil

Questions or comments?

Call 1-800-222-1087

Store at room temperature 68° - 77°F (20° - 25°C).

Theriac Advance Healing Ointment 0.5 oz Tube

THERIAC NDC 11527-325-33

Advanced Healing Ointment

Lanolin 35.08%

Skin Protectant

FREE FROM ANTIBIOTIC, PARABENS & PETROLEUM-BASED INGREDIENTS

NET WT 0.5 OZ (15g)

Theriac Advance Healing Ointment 0.5 OZ Carton

THERIAC NDC 11527-325-33

Advance Healing Ointment

Lanolin 35.08%

Skin Protectant

FREE FROM ANTIBIOBTICS, PARABENS & PETROLEUM-BASED INGREDIENTS

NET WT 0.5 OZ (15g)